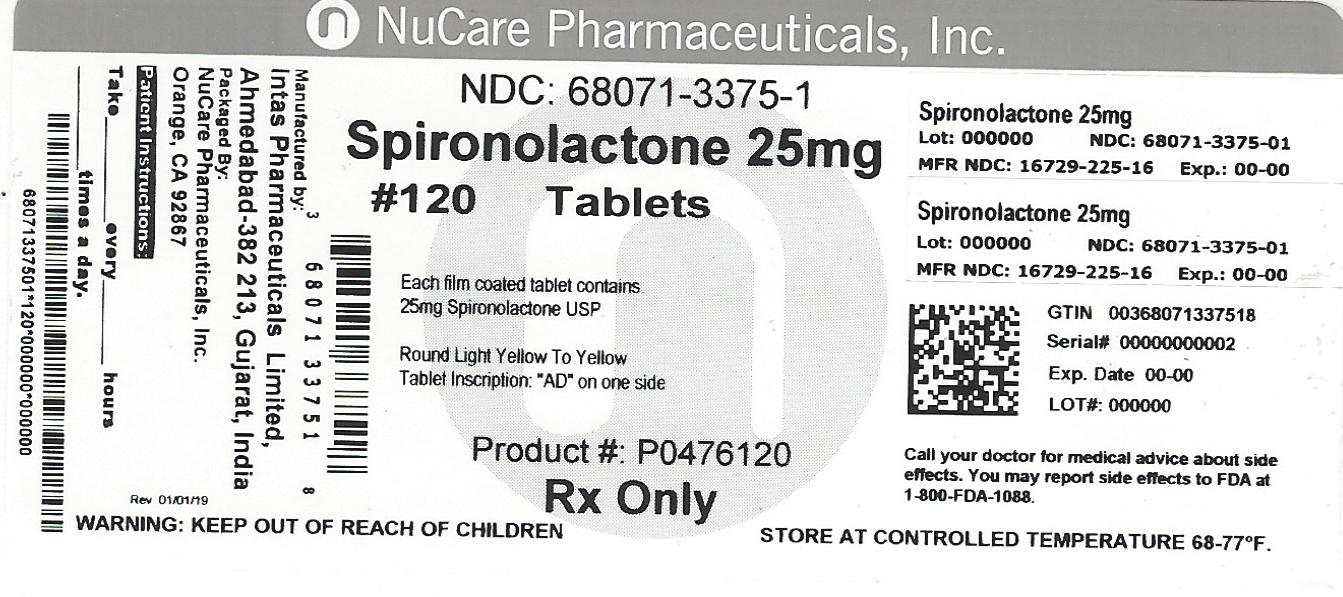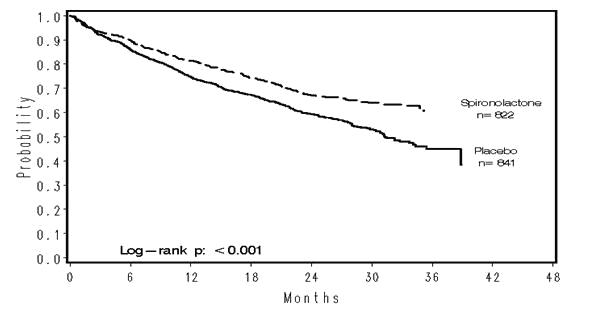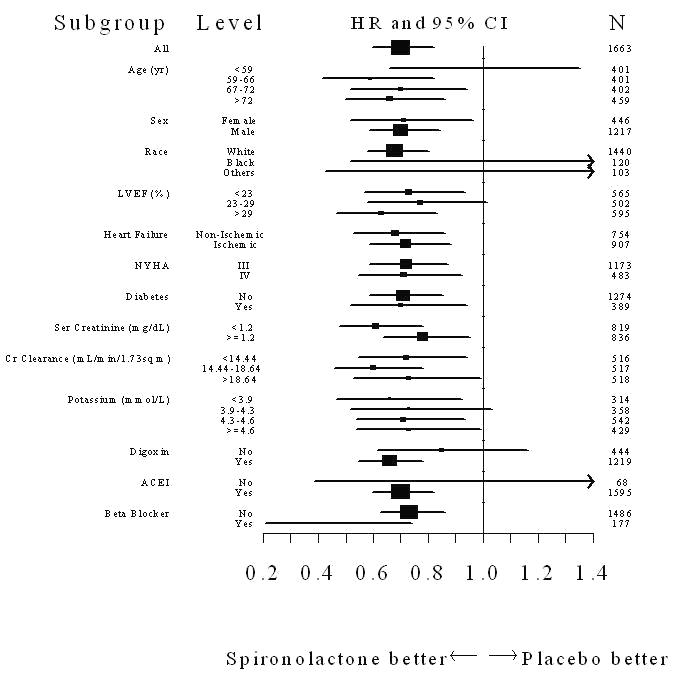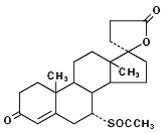 DRUG LABEL: Spironolactone
NDC: 68071-3375 | Form: TABLET, FILM COATED
Manufacturer: NuCare Pharmaceuticals, Inc.
Category: prescription | Type: HUMAN PRESCRIPTION DRUG LABEL
Date: 20240710

ACTIVE INGREDIENTS: SPIRONOLACTONE 25 mg/1 1
INACTIVE INGREDIENTS: LACTOSE MONOHYDRATE; DIBASIC CALCIUM PHOSPHATE DIHYDRATE; POVIDONE K25; PEPPERMINT OIL; TALC; STARCH, CORN; SILICON DIOXIDE; MAGNESIUM STEARATE; HYPROMELLOSES; POLYETHYLENE GLYCOL 400; TITANIUM DIOXIDE; FERRIC OXIDE YELLOW

Spironolactone tablets, USP

WARNING

Spironolactone has been shown to be a tumorigen in chronic toxicity studies in rats (see Precautions). Spironolactone should be used only in those conditions described under Indications and Usage. Unnecessary use of this drug should be avoided.

DESCRIPTION

Spironolactone tablets USP, for oral administration contain 25 mg, 50 mg, or 100 mg of the aldosterone antagonist spironolactone, 17-hydroxy-7α-mercapto-3-oxo-17α-pregn-4-ene-21-carboxylic acid γ-lactone acetate, which has the following structural formula:

Spironolactone is practically insoluble in water, soluble in alcohol, and freely soluble in benzene and in chloroform.

Inactive ingredients include lactose monohydrate, dibasic calcium phosphate, povidone, peppermint oil, purified talc, pregelatinised starch, colloidal anhydrous silica, magnesium stearate, hypromellose, polyethylene glycol 400, titanium dioxide and iron oxide yellow. In addition, iron oxide red (50 mg and 100 mg tablets) is included in the film coating of specific strengths.

ACTIONS / CLINICAL PHARMACOLOGY

Mechanism of action: Spironolactone is a specific pharmacologic antagonist of aldosterone, acting primarily through competitive binding of receptors at the aldosterone-dependent sodium-potassium exchange site in the distal convoluted renal tubule. Spironolactone causes increased amounts of sodium and water to be excreted, while potassium is retained. Spironolactone acts both as a diuretic and as an antihypertensive drug by this mechanism. It may be given alone or with other diuretic agents that act more proximally in the renal tubule.

Aldosterone antagonist activity: Increased levels of the mineralocorticoid, aldosterone, are present in primary and secondary hyperaldosteronism. Edematous states in which secondary aldosteronism is usually involved include congestive heart failure, hepatic cirrhosis, and nephrotic syndrome. By competing with aldosterone for receptor sites, spironolactone provides effective therapy for the edema and ascites in those conditions. Spironolactone counteracts secondary aldosteronism induced by the volume depletion and associated sodium loss caused by active diuretic therapy.

Spironolactone is effective in lowering the systolic and diastolic blood pressure in patients with primary hyperaldosteronism. It is also effective in most cases of essential hypertension, despite the fact that aldosterone secretion may be within normal limits in benign essential hypertension.

Through its action in antagonizing the effect of aldosterone, spironolactone inhibits the exchange of sodium for potassium in the distal renal tubule and helps to prevent potassium loss.

Spironolactone has not been demonstrated to elevate serum uric acid, to precipitate gout, or to alter carbohydrate metabolism.

PHARMACOKINETICS

Pharmacokinetics: Spironolactone is rapidly and extensively metabolized. Sulfur-containing products are the predominant metabolites and are thought to be primarily responsible, together with spironolactone, for the therapeutic effects of the drug. The following pharmacokinetic data were obtained from 12 healthy volunteers following the administration of 100 mg of spironolactone (film-coated tablets) daily for 15 days. On the 15th day, spironolactone was given immediately after a low-fat breakfast and blood was drawn thereafter.

 | Accumulation Factor: AUC (0–24 hr, day 15)/AUC (0–24 hr, day 1) | Mean Peak Serum Concentration | Mean (SD) Post Steady- State Half-Life
7-α-(thiomethyl) spirolactone (TMS) | 1.25 | 391 ng/mL at 3.2 hr | 13.8 hr (6.4) (terminal)
6-β-hydroxy-7-α-(thiomethyl) spirolactone (HTMS) | 1.50 | 125 ng/mL at 5.1 hr | 15.0 hr (4.0) (terminal)
Canrenone (C) | 1.41 | 181 ng/mL at 4.3 hr | 16.5 hr (6.3) (terminal)
Spironolactone | 1.30 | 80 ng/mL at 2.6 hr | Approximately 1.4 hr (0.5) (β half-life)

The pharmacological activity of spironolactone metabolites in man is not known. However, in the adrenalectomized rat the antimineralocorticoid activities of the metabolites C, TMS, and HTMS, relative to spironolactone were 1.10, 1.28, and 0.32, respectively. Relative to spironolactone, their binding affinities to the aldosterone receptors in rat kidney slices were 0.19, 0.86, and 0.06, respectively.

In humans, the potencies of TMS and 7-α-thiospirolactone in reversing the effects of the synthetic mineralocorticoid, fludrocortisone, on urinary electrolyte composition were 0.33 and 0.26, respectively, relative to spironolactone. However, since the serum concentrations of these steroids were not determined, their incomplete absorption and/or first-pass metabolism could not be ruled out as a reason for their reduced in vivo activities.

Spironolactone and its metabolites are more than 90% bound to plasma proteins. The metabolites are excreted primarily in the urine and secondarily in bile.

The effect of food on spironolactone absorption (two 100 mg spironolactone tablets) was assessed in a single-dose study of 9 healthy, drug-free volunteers. Food increased the bioavailability of unmetabolized spironolactone by almost 100%. The clinical importance of this finding is not known.

CLINICAL STUDIES

Severe heart failure: The Randomized Spironolactone Evaluation Study was a multinational, double-blind study in patients with an ejection fraction of ≤ 35%, a history of New York Heart Association (NYHA) class IV heart failure within 6 months, and class III–IV heart failure at the time of randomization. All patients were required to be taking a loop diuretic and, if tolerated, an ACE inhibitor. Patients with a baseline serum creatinine of >2.5 mg/dL or a recent increase of 25% or with a baseline serum potassium of >5.0 mEq/L were excluded.

Patients were randomized 1:1 to spironolactone 25 mg orally once daily or matching placebo. Follow-up visits and laboratory measurements (including serum potassium and creatinine) were performed every four weeks for the first 12 weeks, then every 3 months for the first year, and then every 6 months thereafter. Dosing could be withheld for serious hyperkalemia or if the serum creatinine increased to >4.0 mg/dL. Patients who were intolerant of the initial dosage regimen had their dose decreased to one tablet every other day at one to four weeks. Patients who were tolerant of one tablet daily at 8 weeks may have had their dose increased to two tablets daily at the discretion of the investigator.

The Randomized Spironolactone Evaluation Study enrolled 1663 patients (3% U.S.) at 195 centers in 15 countries between March 24, 1995, and December 31, 1996. The study population was primarily white (87%, with 7% black, 2% Asian, and 4% other), male (73%), and elderly (median age 67). The median ejection fraction was 0.26. Seventy percent were NYHA class III and 29% class IV. The presumed etiology of heart failure was ischemic in 55%, and non-ischemic in 45%. There was a history of myocardial infarction in 28%, of hypertension in 24%, and of diabetes in 22%. The median baseline serum creatinine was 1.2 mg/dL and the median baseline creatinine clearance was 57 mL/min. The mean daily dose at study end for the patients randomized to spironolactone was 26 mg.

Concomitant medications included a loop diuretic in 100% of patients and an ACE inhibitor in 97%. Other medications used at any time during the study included digoxin (78%), anticoagulants (58%), aspirin (43%), and beta-blockers (15%).

The primary endpoint for The Randomized Spironolactone Evaluation Study was time to all-cause mortality. The Randomized Spironolactone Evaluation Study was terminated early, after a mean follow-up of 24 months, because of significant mortality benefit detected on a planned interim analysis. The survival curves by treatment group are shown in Figure 1.

Figure 1. Survival by Treatment Group in The Randomized Spironolactone Evaluation Study

Spironolactone reduced the risk of death by 30% compared to placebo (p<0.001; 95% confidence interval 18% to 40%). Spironolactone reduced the risk of cardiac death, primarily sudden death, and death from progressive heart failure by 31% compared to placebo (p <0.001; 95% confidence interval 18% to 42%).

Spironolactone also reduced the risk of hospitalization for cardiac causes (defined as worsening heart failure, angina, ventricular arrhythmias, or myocardial infarction) by 30% (p <0.001 95% confidence interval 18% to 41%). Changes in NYHA class were more favorable with spironolactone: In the spironolactone group, NYHA class at the end of the study improved in 41% of patients and worsened in 38% compared to improved in 33% and worsened in 48% in the placebo group (p <0.001).

Mortality hazard ratios for some subgroups are shown in Figure 2. The favorable effect of spironolactone on mortality appeared similar for both genders and all age groups except patients younger than 55; there were too few non-whites in The Randomized Spironolactone Evaluation Study to draw any conclusions about differential effects by race. Spironolactone's benefit appeared greater in patients with low baseline serum potassium levels and less in patients with ejection fractions <0.2. These subgroup analyses must be interpreted cautiously.

Figure 2. Hazard Ratios of All-Cause Mortality by Subgroup in The Randomized Spironolactone Evaluation Study

Figure 2: The size of each box is proportional to the sample size as well as the event rate. LVEF denotes left ventricular ejection fraction, Ser Creatinine denotes serum creatinine, Cr Clearance denotes creatinine clearance, and ACEI denotes angiotensin-converting enzyme inhibitor.

INDICATIONS AND USAGE

Spironolactone tablets are indicated in the management of:

Primary hyperaldosteronism for:

Establishing the diagnosis of primary hyperaldosteronism by therapeutic trial.

Short-term preoperative treatment of patients with primary hyperaldosteronism.

Long-term maintenance therapy for patients with discrete aldosterone-producing adrenal adenomas who are judged to be poor operative risks or who decline surgery.

Long-term maintenance therapy for patients with bilateral micro or macronodular adrenal hyperplasia (idiopathic hyperaldosteronism).

Edematous conditions for patients with:

Congestive heart failure: For the management of edema and sodium retention when the patient is only partially responsive to, or is intolerant of, other therapeutic measures. Spironolactone tablets are also indicated for patients with congestive heart failure taking digitalis when other therapies are considered inappropriate.

Cirrhosis of the liver accompanied by edema and/or ascites: Aldosterone levels may be exceptionally high in this condition. Spironolactone tablets are indicated for maintenance therapy together with bed rest and the restriction of fluid and sodium.

Nephrotic syndrome: For nephrotic patients when treatment of the underlying disease, restriction of fluid and sodium intake, and the use of other diuretics do not provide an adequate response.

Essential hypertension

Spironolactone tablets are indicated for the treatment of hypertension, to lower blood pressure. Lowering blood pressure reduces the risk of fatal and nonfatal cardiovascular events, primarily strokes and myocardial infarctions. These benefits have been seen in controlled trials of antihypertensive drugs from a wide variety of pharmacologic classes.

Control of high blood pressure should be part of comprehensive cardiovascular risk management, including, as appropriate, lipid control, diabetes management, antithrombotic therapy, smoking cessation, exercise, and limited sodium intake. Many patients will require more than one drug to achieve blood pressure goals. For specific advice on goals and management, see published guidelines, such as those of the National High Blood Pressure Education Program’s Joint National Committee on Prevention, Detection, Evaluation, and Treatment of High Blood Pressure (JNC).

Numerous antihypertensive drugs, from a variety of pharmacologic classes and with different mechanisms of action, have been shown in randomized controlled trials to reduce cardiovascular morbidity and mortality, and it can be concluded that it is blood pressure reduction, and not some other pharmacologic property of the drugs, that is largely responsible for those benefits. The largest and most consistent cardiovascular outcome benefit has been a reduction in the risk of stroke, but reductions in myocardial infarction and cardiovascular mortality also have been seen regularly.

Elevated systolic or diastolic pressure causes increased cardiovascular risk, and the absolute risk increase per mmHg is greater at higher blood pressures, so that even modest reductions of severe hypertension can provide substantial benefit. Relative risk reduction from blood pressure reduction is similar across populations with varying absolute risk, so the absolute benefit is greater in patients who are at higher risk independent of their hypertension (for example, patients with diabetes or hyperlipidemia), and such patients would be expected to benefit from more aggressive treatment to a lower blood pressure goal.

Some antihypertensive drugs have smaller blood pressure effects (as monotherapy) in black patients, and many antihypertensive drugs have additional approved indications and effects (e.g., on angina, heart failure, or diabetic kidney disease). These considerations may guide selection of therapy.

Usually in combination with other drugs, spironolactone tablets are indicated for patients who cannot be treated adequately with other agents or for whom other agents are considered inappropriate.

Hypokalemia

For the treatment of patients with hypokalemia when other measures are considered inappropriate or inadequate. Spironolactone tablets are also indicated for the prophylaxis of hypokalemia in patients taking digitalis when other measures are considered inadequate or inappropriate.

Severe heart failure (NYHA class III – IV)

To increase survival, and to reduce the need for hospitalization for heart failure when used in addition to standard therapy.

Usage in Pregnancy: The routine use of diuretics in an otherwise healthy woman is inappropriate and exposes mother and fetus to unnecessary hazard. Diuretics do not prevent development of toxemia of pregnancy, and there is no satisfactory evidence that they are useful in the treatment of developing toxemia.

Edema during pregnancy may arise from pathologic causes or from the physiologic and mechanical consequences of pregnancy.

Spironolactone tablets are indicated in pregnancy when edema is due to pathologic causes just as it is in the absence of pregnancy (however, see Precautions: Pregnancy). Dependent edema in pregnancy, resulting from restriction of venous return by the expanded uterus, is properly treated through elevation of the lower extremities and use of support hose; use of diuretics to lower intravascular volume in this case is unsupported and unnecessary.

There is hypervolemia during normal pregnancy which is not harmful to either the fetus or the mother (in the absence of cardiovascular disease), but which is associated with edema, including generalized edema, in the majority of pregnant women. If this edema produces discomfort, increased recumbency will often provide relief. In rare instances, this edema may cause extreme discomfort that is not relieved by rest. In these cases, a short course of diuretics may provide relief and may be appropriate.

CONTRAINDICATIONS

Spironolactone is contraindicated for patients with anuria, acute renal insufficiency, significant impairment of renal excretory function, hyperkalemia, Addison’s disease, and with concomitant use of eplerenone.

WARNINGS

Potassium supplementation. Potassium supplementation, either in the form of medication or as a diet rich in potassium, should not ordinarily be given in association with spironolactone therapy. Excessive potassium intake may cause hyperkalemia in patients receiving spironolactone (see Precautions: General).

Concomitant administration of spironolactone with the following drugs or potassium sources may lead to severe hyperkalemia:

- other potassium-sparing diuretics
- ACE inhibitors
- angiotensin II antagonists
- aldosterone blockers
- non-steroidal anti-inflammatory drugs (NSAIDs), e.g., indomethacin
- heparin and low molecular weight heparin
- other drugs or conditions known to cause hyperkalemia
- potassium supplements
- diet rich in potassium
- salt substitutes containing potassium

Spironolactone should not be administered concurrently with other potassium-sparing diuretics. Spironolactone when used with ACE inhibitors or indomethacin, even in the presence of a diuretic, has been associated with severe hyperkalemia. Extreme caution should be exercised when spironolactone is given concomitantly with these drugs.

Hyperkalemia in patients with severe heart failure. Hyperkalemia may be fatal. It is critical to monitor and manage serum potassium in patients with severe heart failure receiving spironolactone. Avoid using other potassium-sparing diuretics. Avoid using oral potassium supplements in patients with serum potassium > 3.5 mEq/L. The Randomized Spironolactone Evaluation Study excluded patients with a serum creatinine > 2.5 mg/dL or a recent increase in serum creatinine > 25%. The recommended monitoring for potassium and creatinine is one week after initiation or increase in dose of spironolactone, monthly for the first 3 months, then quarterly for a year, and then every 6 months. Discontinue or interrupt treatment for serum potassium > 5 mEq/L or for serum creatinine > 4 mg/dL. (See Clinical Studies: Severe heart failure, and Dosage and Administration: Severe heart failure.)

Spironolactone should be used with caution in patients with impaired hepatic function because minor alterations of fluid and electrolyte balance may precipitate hepatic coma.

Lithium generally should not be given with diuretics (see Precautions: Drug interactions).

PRECAUTIONS

GENERAL PRECAUTIONS

General: All patients receiving diuretic therapy should be observed for evidence of fluid or electrolyte imbalance, e.g., hypomagnesemia, hyponatremia, hypochloremic alkalosis, and hyperkalemia.

Serum and urine electrolyte determinations are particularly important when the patient is vomiting excessively or receiving parenteral fluids. Warning signs or symptoms of fluid and electrolyte imbalance, irrespective of cause, include dryness of the mouth, thirst, weakness, lethargy, drowsiness, restlessness, muscle pains or cramps, muscular fatigue, hypotension, oliguria, tachycardia, and gastrointestinal disturbances such as nausea and vomiting. Hyperkalemia may occur in patients with impaired renal function or excessive potassium intake and can cause cardiac irregularities, which may be fatal. Consequently, no potassium supplement should ordinarily be given with spironolactone.

If hyperkalemia is suspected (warning signs include paresthesia, muscle weakness, fatigue, flaccid paralysis of the extremities, bradycardia and shock), an electrocardiogram (ECG) should be obtained. However, it is important to monitor serum potassium levels because mild hyperkalemia may not be associated with ECG changes.

If hyperkalemia is present, spironolactone should be discontinued immediately. With severe hyperkalemia, the clinical situation dictates the procedures to be employed. These may include the intravenous administration of calcium chloride solution, sodium bicarbonate solution and/or the oral or parenteral administration of glucose with a rapid-acting insulin preparation. These are temporary measures to be repeated as required. Cationic exchange resins such as sodium polystyrene sulfonate may be orally or rectally administered. Persistent hyperkalemia may require dialysis.

Reversible hyperchloremic metabolic acidosis, usually in association with hyperkalemia, has been reported to occur in some patients with decompensated hepatic cirrhosis, even in the presence of normal renal function.

Dilutional hyponatremia, manifested by dryness of the mouth, thirst, lethargy, and drowsiness, and confirmed by a low serum sodium level, may be caused or aggravated, especially when spironolactone is administered in combination with other diuretics, and dilutional hyponatremia may occur in edematous patients in hot weather; appropriate therapy is water restriction rather than administration of sodium, except in rare instances when the hyponatremia is life-threatening.

Spironolactone therapy may cause a transient elevation of BUN, especially in patients with pre-existing renal impairment. Spironolactone tablets may cause mild acidosis.

Gynecomastia may develop in association with the use of spironolactone; physicians should be alert to its possible onset. The development of gynecomastia appears to be related to both dosage level and duration of therapy and is normally reversible when spironolactone is discontinued. In rare instances, some breast enlargement may persist when spironolactone is discontinued.

Somnolence and dizziness have been reported to occur in some patients. Caution is advised when driving or operating machinery until the response to initial treatment has been determined.

PATIENT COUNSELING INFORMATION

Information for patients: Patients who receive spironolactone should be advised to avoid potassium supplements and foods containing high levels of potassium, including salt substitutes.

LABORATORY TESTS

Laboratory tests: Periodic determination of serum electrolytes to detect possible electrolyte imbalance should be done at appropriate intervals, particularly in the elderly and those with significant renal or hepatic impairments.

Drug interactions:

ACE inhibitors: Concomitant administration of ACE inhibitors with potassium-sparing diuretics has been associated with severe hyperkalemia.

Angiotensin II antagonists, aldosterone blockers, heparin, low molecular weight heparin, and other drugs known to cause hyperkalemia: Concomitant administration may lead to severe hyperkalemia.

Alcohol, barbiturates, or narcotics: Potentiation of orthostatic hypotension may occur.

Corticosteroids, ACTH: Intensified electrolyte depletion, particularly hypokalemia, may occur.

Pressor amines (e.g., norepinephrine): Spironolactone reduces the vascular responsiveness to norepinephrine. Therefore, caution should be exercised in the management of patients subjected to regional or general anesthesia while they are being treated with spironolactone.

Skeletal muscle relaxants, nondepolarizing (e.g., tubocurarine): Possible increased responsiveness to the muscle relaxant may result.

Lithium: Lithium generally should not be given with diuretics. Diuretic agents reduce the renal clearance of lithium and add a high risk of lithium toxicity.

Nonsteroidal anti-inflammatory drugs (NSAIDs): In some patients, the administration of an NSAID can reduce the diuretic, natriuretic, and antihypertensive effect of loop, potassium-sparing and thiazide diuretics. Combination of NSAIDs, e.g., indomethacin, with potassium-sparing diuretics has been associated with severe hyperkalemia. Therefore, when spironolactone and NSAIDs are used concomitantly, the patient should be observed closely to determine if the desired effect of the diuretic is obtained.

Digoxin: Spironolactone has been shown to increase the half-life of digoxin. This may result in increased serum digoxin levels and subsequent digitalis toxicity. It may be necessary to reduce the maintenance and digitalization doses when spironolactone is administered, and the patient should be carefully monitored to avoid over- or under- digitalization.

Cholestyramine: Hyperkalemic metabolic acidosis has been reported in patients given spironolactone concurrently with cholestyramine.

DRUG AND OR LABORATORY TEST INTERACTIONS

Drug/Laboratory test interactions: Several reports of possible interference with digoxin radioimmunoassay by spironolactone, or its metabolites, have appeared in the literature. Neither the extent nor the potential clinical significance of its interference (which may be assay-specific) has been fully established.

CARCINOGENESIS AND MUTAGENESIS AND IMPAIRMENT OF FERTILITY

Carcinogenesis, mutagenesis, impairment of fertility: Orally administered spironolactone has been shown to be a tumorigen in dietary administration studies performed in rats, with its proliferative effects manifested on endocrine organs and the liver. In an 18-month study using doses of about 50, 150, and 500 mg/kg/day, there were statistically significant increases in benign adenomas of the thyroid and testes and, in male rats, a dose-related increase in proliferative changes in the liver (including hepatocytomegaly and hyperplastic nodules). In a 24-month study in which the same strain of rat was administered doses of about 10, 30, 100, and 150 mg spironolactone/kg/day, the range of proliferative effects included significant increases in hepatocellular adenomas and testicular interstitial cell tumors in males, and significant increases in thyroid follicular cell adenomas and carcinomas in both sexes. There was also a statistically significant, but not dose-related, increase in benign uterine endometrial stromal polyps in females.

A dose-related (above 20 mg/kg/day) incidence of myelocytic leukemia was observed in rats fed daily doses of potassium canrenoate (a compound chemically similar to spironolactone and whose primary metabolite, canrenone, is also a major product of spironolactone in man) for a period of one year. In two-year studies in the rat, oral administration of potassium canrenoate was associated with myelocytic leukemia and hepatic, thyroid, testicular, and mammary tumors.

Neither spironolactone nor potassium canrenoate produced mutagenic effects in tests using bacteria or yeast. In the absence of metabolic activation, neither spironolactone nor potassium canrenoate has been shown to be mutagenic in mammalian tests in vitro. In the presence of metabolic activation, spironolactone has been reported to be negative in some mammalian mutagenicity tests in vitro and inconclusive (but slightly positive) for mutagenicity in other mammalian tests in vitro. In the presence of metabolic activation, potassium canrenoate has been reported to test positive for mutagenicity in some mammalian tests in vitro, inconclusive in others, and negative in still others.

In a three-litter reproduction study in which female rats received dietary doses of 15 and 50 mg spironolactone/kg/day, there were no effects on mating and fertility, but there was a small increase in incidence of stillborn pups at 50 mg/kg/day. When injected into female rats (100 mg/kg/day for 7 days, i.p.), spironolactone was found to increase the length of the estrous cycle by prolonging diestrus during treatment and inducing constant diestrus during a two-week post-treatment observation period. These effects were associated with retarded ovarian follicle development and a reduction in circulating estrogen levels, which would be expected to impair mating, fertility and fecundity. Spironolactone (100 mg/kg/day), administered i.p. to female mice during a two-week cohabitation period with untreated males, decreased the number of mated mice that conceived (effect shown to be caused by an inhibition of ovulation) and decreased the number of implanted embryos in those that became pregnant (effect shown to be caused by an inhibition of implantation), and at 200 mg/kg, also increased the latency period to mating.

PREGNANCY

TERATOGENIC EFFECTS

Pregnancy: Teratogenic effects. Pregnancy Category C. Teratology studies with spironolactone have been carried out in mice and rabbits at doses of up to 20 mg/kg/day. On a body surface area basis, this dose in the mouse is substantially below the maximum recommended human dose and, in the rabbit, approximates the maximum recommended human dose. No teratogenic or other embryotoxic effects were observed in mice, but the 20 mg/kg dose caused an increased rate of resorption and a lower number of live fetuses in rabbits. Because of its antiandrogenic activity and the requirement of testosterone for male morphogenesis, spironolactone may have the potential for adversely affecting sex differentiation of the male during embryogenesis. When administered to rats at 200 mg/kg/day between gestation days 13 and 21 (late embryogenesis and fetal development), feminization of male fetuses was observed. Offspring exposed during late pregnancy to 50 and 100 mg/kg/day doses of spironolactone exhibited changes in the reproductive tract including dose-dependent decreases in weights of the ventral prostate and seminal vesicle in males, ovaries and uteri that were enlarged in females, and other indications of endocrine dysfunction, that persisted into adulthood. There are no adequate and well-controlled studies with spironolactone in pregnant women. Spironolactone has known endocrine effects in animals including progestational and antiandrogenic effects. The antiandrogenic effects can result in apparent estrogenic side effects in humans, such as gynecomastia. Therefore, the use of spironolactone in pregnant women requires that the anticipated benefit be weighed against the possible hazards to the fetus.

NURSING MOTHERS

Nursing mothers: Canrenone, a major (and active) metabolite of spironolactone, appears in human breast milk. Because spironolactone has been found to be tumorigenic in rats, a decision should be made whether to discontinue the drug, taking into account the importance of the drug to the mother. If use of the drug is deemed essential, an alternative method of infant feeding should be instituted.

PEDIATRIC USE

Pediatric use: Safety and effectiveness in pediatric patients have not been established.

ADVERSE REACTIONS

The following adverse reactions have been reported and, within each category (body system), are listed in order of decreasing severity.

Digestive: Gastric bleeding, ulceration, gastritis, diarrhea and cramping, nausea, vomiting.

Reproductive: Gynecomastia (see Precautions), inability to achieve or maintain erection, irregular menses or amenorrhea, postmenopausal bleeding, breast pain. Carcinoma of the breast has been reported in patients taking spironolactone but a cause and effect relationship has not been established.

Hematologic: Leukopenia (including agranulocytosis), thrombocytopenia.

Hypersensitivity: Fever, urticaria, maculopapular or erythematous cutaneous eruptions, anaphylactic reactions, vasculitis.

Metabolism: Hyperkalemia, electrolyte disturbances (see Warnings and Precautions).

Musculoskeletal: Leg cramps.

Nervous system /psychiatric: Lethargy, mental confusion, ataxia, dizziness, headache, drowsiness.

Liver / biliary: A very few cases of mixed cholestatic/hepatocellular toxicity, with one reported fatality, have been reported with spironolactone administration.

Renal: Renal dysfunction (including renal failure).

Skin: Stevens-Johnson Syndrome (SJS), toxic epidermal necrolysis (TEN), drug rash with eosinophilia and systemic symptoms (DRESS), alopecia, pruritis.

OVERDOSAGE

The oral LD50 of spironolactone is greater than 1000 mg/kg in mice, rats, and rabbits.

Acute overdosage of spironolactone may be manifested by drowsiness, mental confusion, maculopapular or erythematous rash, nausea, vomiting, dizziness, or diarrhea. Rarely, instances of hyponatremia, hyperkalemia, or hepatic coma may occur in patients with severe liver disease, but these are unlikely due to acute overdosage. Hyperkalemia may occur, especially in patients with impaired renal function.

Treatment: Induce vomiting or evacuate the stomach by lavage. There is no specific antidote. Treatment is supportive to maintain hydration, electrolyte balance, and vital functions.

Patients who have renal impairment may develop spironolactone-induced hyperkalemia. In such cases, spironolactone should be discontinued immediately. With severe hyperkalemia, the clinical situation dictates the procedures to be employed. These may include the intravenous administration of calcium chloride solution, sodium bicarbonate solution and/or the oral or parenteral administration of glucose with a rapid-acting insulin preparation. These are temporary measures to be repeated as required. Cationic exchange resins such as sodium polystyrene sulfonate may be orally or rectally administered. Persistent hyperkalemia may require dialysis.

DOSAGE AND ADMINISTRATION

Primary hyperaldosteronism. Spironolactone tablets may be employed as an initial diagnostic measure to provide presumptive evidence of primary hyperaldosteronism while patients are on normal diets.

Long test: Spironolactone is administered at a daily dosage of 400 mg for three to four weeks. Correction of hypokalemia and of hypertension provides presumptive evidence for the diagnosis of primary hyperaldosteronism.

Short test: Spironolactone is administered at a daily dosage of 400 mg for four days. If serum potassium increases during spironolactone administration but drops when spironolactone is discontinued, a presumptive diagnosis of primary hyperaldosteronism should be considered.

After the diagnosis of hyperaldosteronism has been established by more definitive testing procedures, spironolactone may be administered in doses of 100 to 400 mg daily in preparation for surgery. For patients who are considered unsuitable for surgery, spironolactone may be employed for long-term maintenance therapy at the lowest effective dosage determined for the individual patient.

Edema in adults (congestive heart failure, hepatic cirrhosis, or nephrotic syndrome). An initial daily dosage of 100 mg of spironolactone administered in either single or divided doses is recommended, but may range from 25 to 200 mg daily. When given as the sole agent for diuresis, spironolactone should be continued for at least five days at the initial dosage level, after which it may be adjusted to the optimal therapeutic or maintenance level administered in either single or divided daily doses. If, after five days, an adequate diuretic response to spironolactone has not occurred, a second diuretic that acts more proximally in the renal tubule may be added to the regimen. Because of the additive effect of spironolactone when administered concurrently with such diuretics, an enhanced diuresis usually begins on the first day of combined treatment; combined therapy is indicated when more rapid diuresis is desired. The dosage of spironolactone should remain unchanged when other diuretic therapy is added.

Essential hypertension. For adults, an initial daily dosage of 50 to 100 mg of spironolactone administered in either single or divided doses is recommended. Spironolactone may also be given with diuretics that act more proximally in the renal tubule or with other antihypertensive agents. Treatment with spironolactone should be continued for at least two weeks, since the maximum response may not occur before this time. Subsequently, dosage should be adjusted according to the response of the patient.

Hypokalemia. Spironolactone in a dosage ranging from 25 mg to 100 mg daily is useful in treating a diuretic-induced hypokalemia, when oral potassium supplements or other potassium-sparing regimens are considered inappropriate.

Severe heart failure in conjunction with standard therapy (NYHA class III – IV). Treatment should be initiated with spironolactone 25 mg once daily if the patient's serum potassium is ≤5.0 mEq/L and the patient's serum creatinine is ≤ 2.5 mg/dL. Patients who tolerate 25 mg once daily may have their dosage increased to 50 mg once daily as clinically indicated. Patients who do not tolerate 25 mg once daily dose may have their dosage reduced to 25 mg every other day. See Warnings: Hyperkalemia in patients with severe heart failure for advice on monitoring serum potassium and serum creatinine.

HOW SUPPLIED

Spironolactone Tablets USP 25 mg tablets are Light yellow to yellow colored, round, biconvex, film coated tablets with inscription AD on one side and plain on the other side having faint odour of peppermint, supplied as:

Store at 20° to 25°C (68° to 77°F) [See USP Controlled Room Temperature]

bottles of 30 NDC 68071-3375-3

bottles of 60 NDC 68071-3375-6

bottles of 90 NDC 68071-3375-9

bottles of 120 NDC 68071-3375-1

bottles of 180 NDC 68071-3375-8

Protect from light. Dispense in tight, Light-resistant containers.

Manufactured For:
Accord Healthcare, Inc.,
1009 Slater Road,
Suite 210-B,
Durham, NC 27703,
USA.
Manufactured By:
Intas Pharmaceuticals Limited,
Plot No 5 to 12, Pharmez,
Sarkhej-Bavla, National Highway No 8-A,
Near Village Matoda, Tal Sanand,
Ahmedabad - 382 213, Gujarat, India
51 2267 0 700753
Issued November 2016.